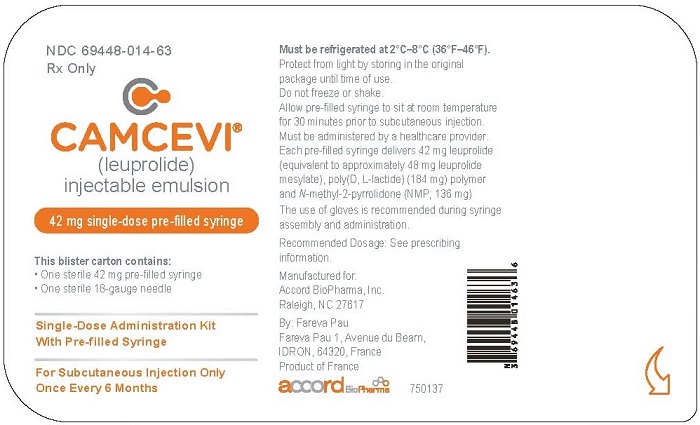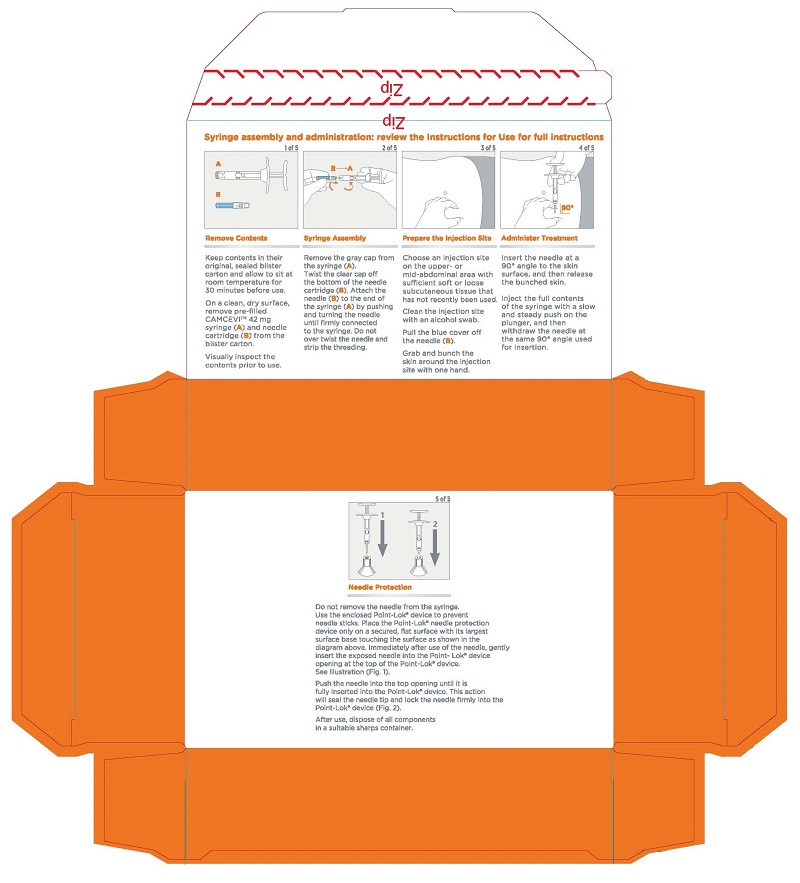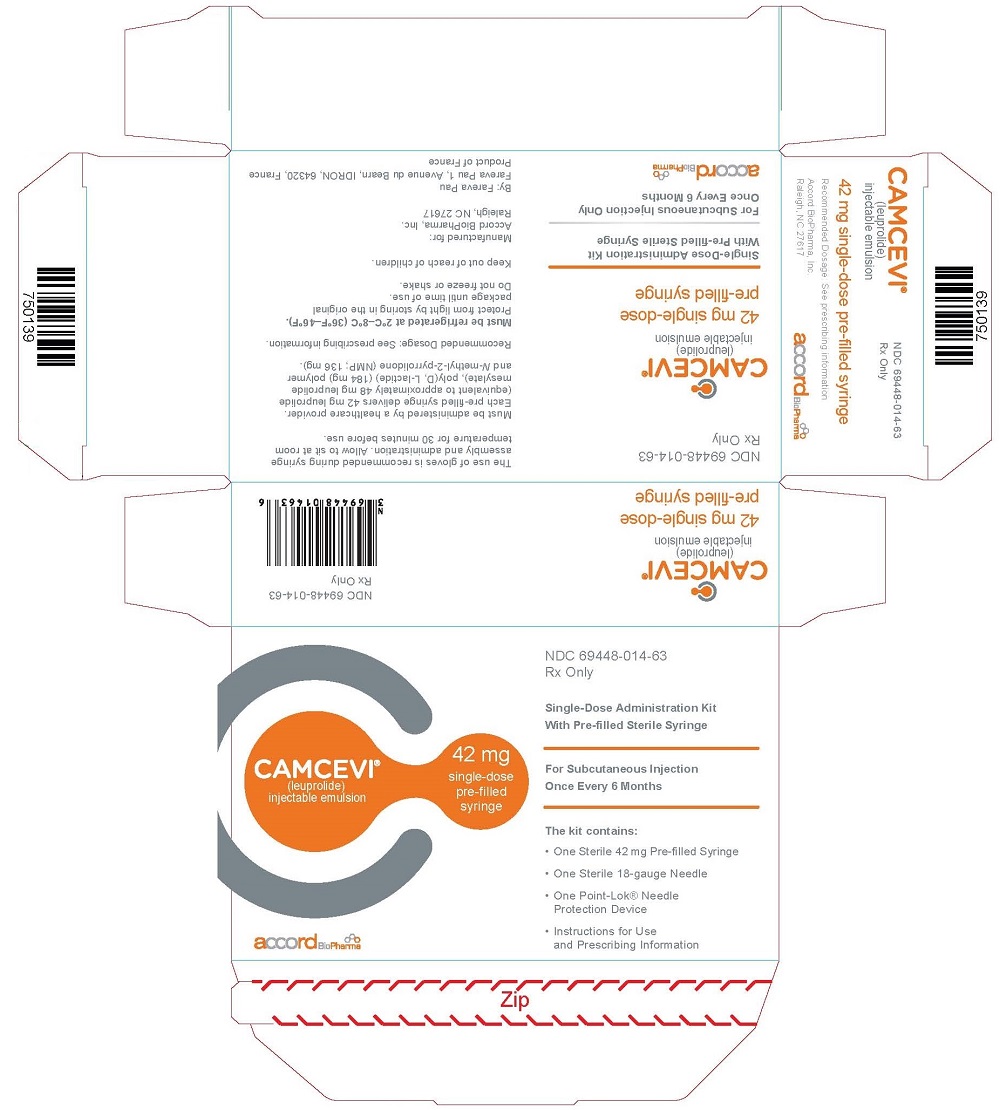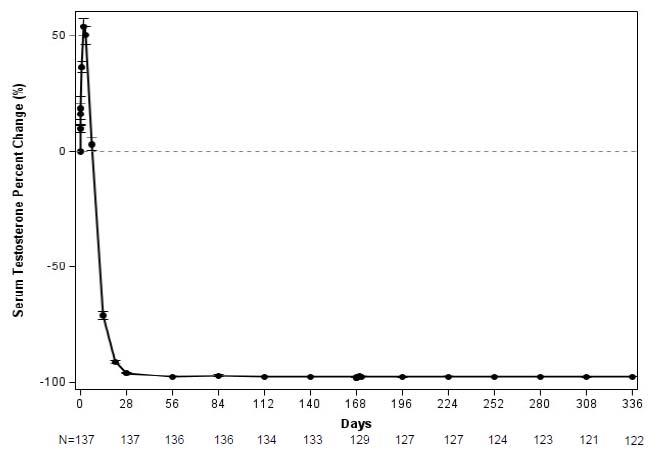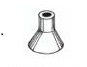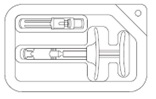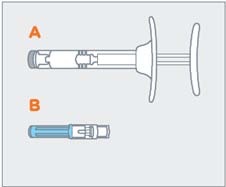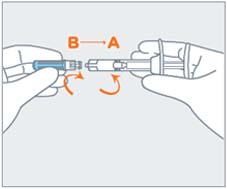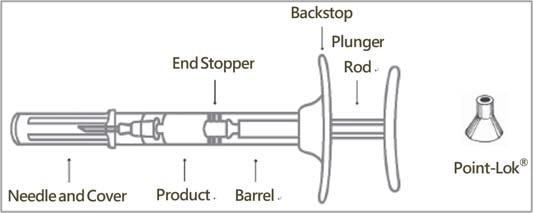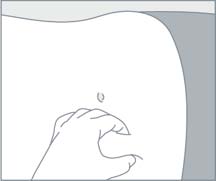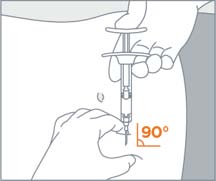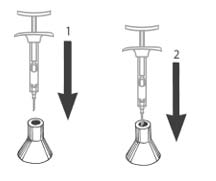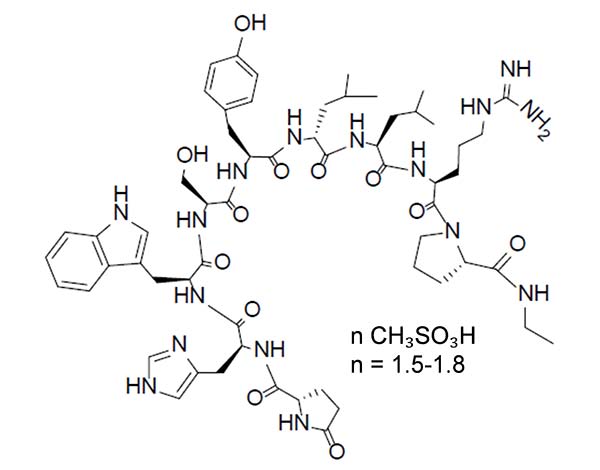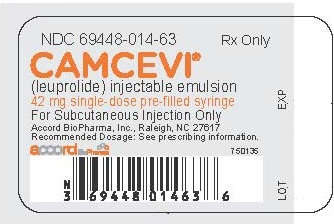 DRUG LABEL: CAMCEVI
NDC: 69448-014 | Form: INJECTION, EMULSION
Manufacturer: Accord BioPharma, Inc.
Category: prescription | Type: HUMAN PRESCRIPTION DRUG LABEL
Date: 20260218

ACTIVE INGREDIENTS: LEUPROLIDE MESYLATE 42 mg/0.37 g
INACTIVE INGREDIENTS: POLYLACTIDE 184 mg/0.37 g; METHYLPYRROLIDONE 136 mg/0.37 g

HIGHLIGHTS OF PRESCRIBING INFORMATION

These highlights do not include all the information needed to use CAMCEVI®safely and effectively. See full prescribing information for CAMCEVI.
CAMCEVI (leuprolide) injectable emulsion, for subcutaneous use
Initial U.S. Approval: 2021

1 INDICATIONS AND USAGE

CAMCEVI is a gonadotropin-releasing hormone (GnRH) agonist indicated for the treatment of adult patients with advanced prostate cancer.

RECENT MAJOR CHANGES

Dosage and Administration (2.2) 02/2025

Warnings and Precautions (5.6) 09/2025

2 DOSAGE AND ADMINISTRATION

- See Full Prescribing Information for instructions on the preparation and administration of the injectable emulsion in a pre-filled syringe. (2)
- Recommended Dosage: 42 mg subcutaneously every 6 months. (2)

3 DOSAGE FORMS AND STRENGTHS

- Injectable emulsion: 42 mg (3)

4 CONTRAINDICATIONS

- Hypersensitivity to GnRH, GnRH agonist analogs, or any of the components of CAMCEVI. (4)

5 WARNINGS AND PRECAUTIONS

- Tumor Flare: Transient worsening of bone pain, uretral obstruction, spinal cord compression, or the occurrence of additional signs and symptoms of prostate cancer may develop during the first few weeks of treatment. Monitor patients closely and manage symptoms. (5.1)
- Hyperglycemia and Diabetes: Hyperglycemia and an increased risk of developing diabetes have been reported in men receiving GnRH agonists. Monitor blood glucose levels and manage according to current clinical practice. (5.2)
- Cardiovascular Diseases: Increased risk of myocardial infarction, sudden cardiac death, and stroke has been reported in men receiving GnRH agonists. Monitor for cardiovascular disease and manage according to current clinical practice. (5.3)
- QT/QTc Prolongation: Androgen deprivation therapy may prolong the QT interval. Consider periodic monitoring of electrocardiograms and electrolytes. (5.4)
- Convulsions: Manage convulsions according to the current clinical practice. (5.5)
- Severe Cutaneous Adverse Reactions: CAMCEVI can cause severe cutaneous adverse reactions (SCARs), including Stevens-Johnson syndrome/toxic epidermal necrolysis. Interrupt CAMCEVI if signs or symptoms of SCARs develop. Permanently discontinue if SCARs are confirmed. (5.6)
- Embryo-Fetal Toxicity: CAMCEVI may cause fetal harm. (5.8, 8.1)

6 ADVERSE REACTIONS

The most common (≥5%) adverse reactions were hot flushes, hypertension, injection site reactions, fatigue, upper respiratory tract infections, musculoskeletal pain, pain in extremity, arthralgia, micturition urgency, nocturia, and dizziness. (6.1)

To report SUSPECTED ADVERSE REACTIONS, contact Accord BioPharma Inc. at 1-866-941-7875 or FDA at 1-800-FDA-1088 orwww.fda.gov/medwatch

8 USE IN SPECIFIC POPULATIONS

- Females and males of reproductive potential: CAMCEVI may impair fertility. (8.3)
- Safety and effectiveness in pediatric patients have not been established. (8.4)

FULL PRESCRIBING INFORMATION

1 INDICATIONS AND USAGE

CAMCEVI is indicated for the treatment of adult patients with advanced prostate cancer.

2 DOSAGE AND ADMINISTRATION

2.1 Recommended Dosage

The recommended dose of CAMCEVI is 42 mg administered subcutaneously once every 6 months.

2.2 Preparation and Administration

CAMCEVI must be administered by a healthcare provider.

Important:Read the instructions completely before you administer Camcevi for the first time. Do NOT substitute any of the components from the kit for administration.

CAMCEVI is packaged in a blister in the kit. Check to make sure the kit contains:

- One sterile, single-dose pre-filled syringe with plunger rod and backstop
- One sterile 18-gauge, 5/8-inch needle
- One Point-Lok®Needle Protection Device
- Prescribing Information

Follow the detailed instructions to ensure correct preparation of CAMCEVI prior to administration:

STEP 1
Remove CAMCEVI kit from refrigerator.
Keep the contents in their original, sealed blister carton and allow to sit at room temperature for 30 minutes before use.
Return to refrigerator after 30 minutes if not used.

STEP 2
On a clean, dry surface, open carton and remove the contents. Examine all contents of the package. Do not use if any component is damaged.
Check the expiration date on the syringe. Do not use if the expiration date has passed.
The use of gloves is recommended during syringe assembly and administration.

STEP 3
Remove pre-filled syringe (A) and needle cartridge (B) from the blister tray.
Visually inspect the syringe for particulate matter prior to administration. The emulsion should appear off-white to pale yellow, viscous, and opalescent. Do not use if particulate matter is observed prior to administration.

STEP 4
Remove the gray cap from the syringe (A).
Twist the clear cap off the bottom of the needle cartridge (B).
Attach the needle (B) to the end of the syringe (A) by pushing and turning the needle until firmly connected to the syringe.
Do not over twist the needle and strip the threading.
See figure of assembled pre-filled syringe below.

STEP 5
Choose an injection site on the upper- or mid-abdominal area with sufficient soft or loose subcutaneous tissue that has not recently been used.
Clean the injection site with an alcohol swab.
Do NOTinject in areas with brawny or fibrous subcutaneous tissue or locations that can be rubbed or compressed (i.e., with a belt or clothing waistband). In addition, avoid applying heat directly to the site of Camcevi injection.

STEP 6
Pull the blue cover off the needle (B). Use standard sharps safety techniques to avoid needle sticks.

STEP 7
Use standard aseptic technique when performing the injection.
Grab and bunch the skin around the injection site with one hand.
Insert the needle at a 90° angle to the skin surface, and then release the bunched skin.

STEP 8
Inject the full contents of the syringe with a slow and steady push on the plunger, and then withdraw the needle at the same 90° angle used for insertion.

STEP 9
Do not remove the needle from the syringe. Use the enclosed Point-Lok®device to prevent needle sticks.
Retrieve the Point-Lok®needle protection device from the Camcevi kit and place it on a secured, flat surface with its largest surface base touching the surface as shown in the diagram.
Immediately after use of the needle, gently insert the exposed needle into the Point-Lok®device opening at the top of the Point-Lok®device. (see Figure 1)
Push the needle into the top opening until it is fully inserted into the Point-Lok®device. This action will seal the needle tip and lock the needle firmly into the Point-Lok®device. (see Figure 2)

STEP 10
After use, discard all components safely in a suitable sharps container. Dispose of the syringe and contaminated products according to local regulations/procedures.

3 DOSAGE FORMS AND STRENGTHS

Injectable emulsion: 42 mg leuprolide (equivalent to approximately 48 mg leuprolide mesylate) as a sterile, off-white to pale yellow, viscous, and opalescent emulsion in a single-dose, pre-filled syringe for subcutaneous injection.

4 CONTRAINDICATIONS

CAMCEVI is contraindicated in patients known to be hypersensitive to GnRH, GnRH agonist analogs, or any of the excipients in CAMCEVI. Anaphylactic reactions to GnRH agonist analogs have been reported in the medical literature.

5 WARNINGS AND PRECAUTIONS

5.1 Tumor Flare

CAMCEVI, like other GnRH agonists, causes a transient increase in serum levels of testosterone during the first week of treatment, declining thereafter to baseline levels or below by the end of the second week of treatment. Transient worsening of symptoms, or the occurrence of additional signs and symptoms of prostate cancer, may develop during the first few weeks of CAMCEVI treatment. Patients treated with CAMCEVI may experience a temporary increase in bone pain, which can be managed symptomatically.

Cases of ureteral obstruction and spinal cord compression have been observed, which may contribute to paralysis with or without fatal complications.

Patients with metastatic vertebral lesions and/or with urinary tract obstruction should be closely observed during the first few weeks of therapy.

5.2 Hyperglycemia and Diabetes

Hyperglycemia and an increased risk of developing diabetes have been reported in men receiving GnRH agonists. Hyperglycemia may represent the development of diabetes mellitus or worsening of glycemic control in patients with diabetes. Monitor blood glucose and/or glycosylated hemoglobin (HbA1c) periodically in patients receiving a GnRH agonist and manage with current practice for treatment of hyperglycemia or diabetes.

5.3 Cardiovascular Diseases

Increased risk of developing myocardial infarction, sudden cardiac death, and stroke has been reported in association with use of GnRH agonists in men. The risk appears low based on the reported odds ratios, and should be evaluated carefully along with cardiovascular risk factors when determining a treatment for patients with prostate cancer. Patients receiving a GnRH agonist should be monitored for symptoms and signs suggestive of development of cardiovascular disease and be managed according to current clinical practice.

5.4 QT/QTc Prolongation

Androgen deprivation therapy may prolong the QT/QTc interval. Providers should consider whether the benefits of androgen deprivation therapy outweigh the potential risks in patients with congenital long QT syndrome, congestive heart failure, frequent electrolyte abnormalities, and in patients taking drugs known to prolong the QT interval. Electrolyte abnormalities should be corrected. Consider periodic monitoring of electrocardiograms and electrolytes.

5.5 Convulsions

Convulsions have been reported in patients receiving GnRH agonists, like CAMCEVI [see Adverse Reactions (6.2)]. Manage patients receiving a GnRH agonist who experience convulsions according to current clinical practice.

5.6 Severe Cutaneous Adverse Reactions

CAMCEVI can cause severe cutaneous adverse reactions (SCARs), including Stevens-Johnson syndrome/toxic epidermal necrolysis (SJS/TEN), drug reaction with eosinophilia and systemic symptoms (DRESS), and acute generalized exanthematous pustulosis (AGEP). SCARs, including SJS/TEN, DRESS, and AGEP, occurred in patients receiving CAMCEVI or other GnRH agonists; including cases with visceral involvement and/or requiring skin grafts [see Adverse Reactions (6.2)] .

Monitor patients for the development of SCARs.

If a SCAR is suspected, interrupt CAMCEVI until the etiology of the reaction has been determined. Consultation with a dermatologist is recommended. If a SCAR is confirmed, or for other grade 4 skin reactions, permanently discontinue CAMCEVI.

5.7 Laboratory Tests

Monitor serum levels of testosterone following injection of CAMCEVI. In the majority of patients treated with CAMCEVI, testosterone levels increased above baseline during the first week, and then declined thereafter to castration levels (<50 ng/dL) within 4 weeks [see Clinical Studies (14) and Adverse Reactions (6)].

5.8 Embryo-Fetal Toxicity

Based on findings in animal studies and mechanism of action, CAMCEVI can cause fetal harm when administered to a pregnant woman. In animal developmental and reproductive toxicology studies, administration of a monthly formulation of leuprolide on day 6 of pregnancy (sustained exposure was expected throughout the period of organogenesis) caused adverse embryo-fetal toxicity in animals at doses less than the human dose based on body surface area using an estimated daily dose. Advise pregnant patients and females of reproductive potential of the potential risk to the fetus [see Use in Specific Population (8.1), Clinical Pharmacology (12.1)].

6 ADVERSE REACTIONS

The following adverse reactions are discussed in greater detail in other sections of the labeling:

- Tumor Flare [see Warnings and Precautions (5.1)]
- Hyperglycemia and Diabetes [see Warnings and Precautions (5.2)]
- Cardiovascular Diseases [see Warnings and Precautions (5.3)]
- QT/QTc Prolongation [see Warnings and Precautions (5.4)]
- Convulsions [see Warnings and Precautions (5.5)]

6.1 Clinical Trial Experience

Because clinical trials are conducted under widely varying conditions, adverse reaction rates observed in the clinical trials of a drug cannot be directly compared to rates in the clinical trials of another drug and may not reflect the rates observed in practice.

FP01C-13-001
The safety of CAMCEVI was evaluated in an open-label, single-arm, international clinical trial (FP01C-13-001) in patients with advanced prostate cancer. Patients received CAMCEVI administered subcutaneously at a dose of 42 mg on Day 0 and Day 168. Of 137 patients enrolled, 93% received both doses of CAMCEVI.

Serious adverse reactions occurred in 15% of patients who received CAMCEVI, including 1% of patients who experienced subdural hematoma. Fatal adverse reactions occurred in 2% of patients, including cerebrovascular accident (0.7%) and pulmonary embolism (0.7%).

The most common adverse reactions (≥10%) occurring during a median follow-up duration of 336 days were hot flush, hypertension, injection site reactions, upper respiratory tract infections, musculoskeletal pain, fatigue, and pain in extremity.

Table 1 summarizes the adverse reactions in FP01C-13-001.

Table 1. Adverse Reactions Occurring in ≥5% of CAMCEVI in Advanced Prostate Cancer Patients - FP01C-13-001

Adverse Reaction | CAMCEVI; N = 137
 | All Grades (%) | Grade 3-4 (%)
Vascular disorders
Hot flushesa | 50 | 0
Hypertensionb | 15 | 0
General disorders and administration site conditions
Injection site reactionsc | 11 | 0
Fatigued | 10 | 0
Infections and infestations
Upper respiratory tract infectione | 11 | 0
Musculoskeletal and connective tissue disorders
Musculoskeletal painf | 11 | 0
Pain in extremity | 10 | 0
Arthralgia | 7 | 0
Renal and urinary disorders
Micturition urgencyg | 6 | 0
Nocturia | 6 | 0
Nervous system disorders
Dizzinessh | 5 | 0.7

aincludes hot flush and flushing
bincludes hypertension, essential hypertension, and blood pressure increased
cincludes injection site pain, injection site erythema, injection site hemorrhage, injection site nodule, injection site paraesthesia, injection site pruritus, and injection site warmth
dincludes fatigue and asthenia
eincludes upper respiratory tract infection, sinusitis, and nasopharyngitis
fincludes musculoskeletal pain, back pain, and bone pain
gincludes micturition urgency and dysuria
hincludes dizziness, dizziness postural, vertigo, and vertigo positional.

6.2 Postmarketing Experience

The following adverse reactions have been identified during post approval use of CAMCEVI or leuprolide. Because these reactions are reported voluntarily from a population of uncertain size, it is not always possible to reliably estimate their frequency or establish a causal relationship to drug exposure.
During postmarketing surveillance, which includes other dosage forms and other patient populations, the following adverse reactions were reported.
Allergic Conditions: hypersensitivity reactions including anaphylaxis, rash, urticaria, and photosensitivity reactions
Cardiovascular System:hypotension, myocardial infarction, pulmonary embolism
Central/Peripheral Nervous System:convulsion, peripheral neuropathy, spinal fracture/paralysis
Endocrine System:pituitary apoplexy, diabetes
Hepato-biliary disorder:drug-induced liver injury
Hematologic: leukopenia
Psychiatric:mood swings, including depression, suicidal ideation and attempt
Respiratory, thoracic and mediastinal disorder:interstitial lung disease
Musculoskeletal System:decreased bone density, tenosynovitis-like symptoms, fibromyalgia
Skin and Subcutaneous:injection site induration or swelling, SJS/TEN, DRESS, AGEP, dermatitis exfoliative, bullous dermatitis, and erythema multiforme
Urogenital System:prostate pain

8 USE IN SPECIFIC POPULATIONS

8.1 Pregnancy

Risk Summary

Based on findings in animal studies and mechanism of action, CAMCEVI can cause fetal harm when administered to a pregnant woman [see Clinical Pharmacology (12.1)]. There are no available data in pregnant women to inform the drug-associated risk. In animal developmental and reproductive toxicology studies, administration of a monthly formulation of leuprolide on day 6 of pregnancy (sustained exposure was expected throughout the period of organogenesis) caused adverse embryo-fetal toxicity in animals at doses less than the human dose based on body surface area using an estimated daily dose (see data). Advise pregnant patients and females of reproductive potential of the potential risk to the fetus.

Data

Animal Data

Major fetal malformations were observed in developmental and reproductive toxicology studies in rabbits after a single administration of a monthly formulation of leuprolide administered on day 6 of pregnancy at test dosages of 0.00024, 0.0024, and 0.024 mg/kg (approximately 1/1500 to 1/15 the human dose based on body surface area using an estimated daily dose in animals and humans). Since a depot formulation was utilized in the study, a sustained exposure to leuprolide was expected throughout the period of organogenesis and to the end of gestation. Similar studies in rats did not demonstrate an increase in fetal malformations, however, there was increased fetal mortality and decreased fetal weights with the two higher doses of the monthly formulation of leuprolide in rabbits and with the highest dose in rats.

8.2 Lactation

Risk Summary

The safety and efficacy of CAMCEVI have not been established in females. There is no information regarding the presence of leuprolide in human milk, the effects on the breastfed child, or the effects on milk production. Because many drugs are excreted in human milk and because of the potential for serious adverse reactions in a breastfed child, a decision should be made to discontinue breastfeeding or discontinue the drug, taking into account the importance of the drug to the mother.

8.3 Females and Males of Reproductive Potential

Infertility

Males

Based on findings in animals and mechanism of action, CAMCEVI may impair fertility in males of reproductive potential [see Clinical Pharmacology (12.1), Nonclinical Toxicology (13.1) ].

8.4 Pediatric Use

The safety and efficacy of CAMCEVI in pediatric patients have not been established.

8.5 Geriatric Use

Of the 137 patients who received CAMCEVI in the FP01C-13-001 study, 74% were 65 years of age or older, while 37% were 75 years of age or older. No overall differences in safety or effectiveness were observed between these patients and younger patients.

11 DESCRIPTION

CAMCEVI is a sterile formulation of leuprolide mesylate for subcutaneous injection. CAMCEVI is designed to deliver approximately 42 mg of leuprolide over 6 months.

Leuprolide mesylate is a synthetic nonapeptide analog of naturally occurring GnRH and is a GnRH agonist. The analog possesses greater potency than the natural hormone. The chemical name is 5-oxo-L-prolyl-L-histidyl-L-tryptophyl-L-seryl-L-tyrosyl-D-leucyl-L-leucyl-L-arginyl-N-ethyl-L-prolinamide mesylate (salt) with the following structural formula. The pH of 50 mg/mL solution of leuprolide mesylate in water is approximately 5.7.

CAMCEVI is supplied as a kit with a pre-filled, single-dose, sterile syringe for subcutaneous injection. Each pre-filled syringe delivers 42 mg leuprolide (equivalent to approximately 48 mg leuprolide mesylate), poly(D, L-lactide) (184 mg) polymer and N-methyl-2-pyrrolidone (136 mg).

12 CLINICAL PHARMACOLOGY

12.1 Mechanism of Action

Leuprolide, a GnRH agonist, acts as an inhibitor of gonadotropin secretion. Animal and human studies indicate that following an initial stimulation of gonadotropins, chronic administration of leuprolide results in suppression of ovarian and testicular steroidogenesis. This effect is reversible upon discontinuation of drug therapy.

12.2 Pharmacodynamics

Mean serum testosterone concentrations transiently increased, then fell to below castrate threshold levels (≤ 50 ng/dL) within 3 weeks following administration of the dose of leuprolide, and generally remained below castrate thresholds levels throughout treatment.

In humans, subcutaneous administration of single daily doses of leuprolide result in an initial increase in circulating levels of LH and FSH, leading to a transient increase in levels of the gonadal steroids (testosterone and dihydrotestosterone in males). However, continuous daily administration of leuprolide results in decreased levels of LH and FSH. In males, testosterone is reduced to below castration levels. These decreases generally occur within 2 to 4 weeks after initiation of treatment, and castration levels of testosterone in prostatic cancer patients have been demonstrated for periods of up to 5 years.

12.3 Pharmacokinetics

Leuprolide concentration is variable, exhibiting an initial rapid increase followed by a rapid decline over the first 3 days before reaching steady concentrations for the duration of the dosing interval. The mean serum leuprolide Cmaxwas 94.5 and 99 ng/mL following the first and second doses of CAMCEVI, respectively. The mean serum concentration was maintained at 0.497–2.57 and 0.507–2.39 ng/ml after Day 3 post the first and second doses, respectively. The mean AUC0-6 monwas 224 and 268 day.ng/mL following the first and second doses of CAMCEVI, respectively.

Absorption

The median Tmaxof leuprolide was 3.2 and 2.1 hours following the first and second doses of CAMCEVI, respectively

Distribution

The mean steady-state volume of distribution of leuprolide was 27 L following an intravenous bolus in healthy male volunteers. Protein binding of leuprolide ranged from 43% to 49% in vitro.

Elimination

The mean systemic clearance was 7.6 L/h and terminal elimination half-life of approximately 3 hours following an intravenous bolus of leuprolide in healthy male volunteers.

Metabolism

Administration of radiolabeled leuprolide was metabolized to smaller inactive peptides which may then be further catabolized.

Excretion

Excretion of leuprolide has not been evaluated with CAMCEVI.

Specific Populations

No clinically significant differences in the systemic exposure of leuprolide were observed based on age (51 to 88 years), race/ethnicity (White, Black, Asian), or body weight (54 to 134 kg). The effect of renal or hepatic impairment on the pharmacokinetics of leuprolide has not been evaluated.

13 NONCLINICAL TOXICOLOGY

13.1 Carcinogenesis, Mutagenesis, Impairment of Fertility

Two-year carcinogenicity studies were conducted with leuprolide in rats and mice. In rats, a dose-related increase of benign pituitary hyperplasia and benign pituitary adenomas was noted at 24 months when the drug was administered subcutaneously at high daily doses (0.6 to 4 mg/kg). There was a significant but not dose-related increase of pancreatic islet-cell adenomas in females and of testicular interstitial cell adenomas in males (highest incidence in the low dose group). In mice, no pituitary abnormalities were observed at a dose as high as 60 mg/kg for 2 years. Patients have been treated with leuprolide for up to 3 years with doses as high as 10 mg/day and for 2 years with doses as high as 20 mg/day without demonstrable pituitary abnormalities.

Mutagenicity studies have been performed with leuprolide using bacterial and mammalian systems. These studies provided no evidence of mutagenic potential.

Leuprolide may reduce male and female fertility. Administration of leuprolide to male and female rats at doses of 0.024, 0.24, and 2.4 mg/kg as monthly depot formulation for up to 3 months (approximately as low as 1/30 of the human dose based on body surface area using an estimated daily dose in animals and humans) caused atrophy of the reproductive organs, and suppression of reproductive function. These changes were reversible upon cessation of treatment.

14 CLINICAL STUDIES

The efficacy of CAMCEVI was evaluated in an open label, single arm, multinational study FP01C-13-001 (NCT02234115) in patients with advanced prostate carcinoma who have a baseline morning serum testosterone level >150 ng/dL and Eastern Cooperative Oncology Group performance status ≤ 2. CAMCEVI was administered subcutaneously at a dose of 42 mg initially on Day 0 and on Week 24.

The population (n = 137) had a median age of 71 years (range 51 to 88) and was 90% White, 6% Black, and 4% Asian. Disease stage was distributed as follows: 23% metastatic (M1), 27% locally advanced (T3/4 NX M0 or any T N1 M0), 26% localized (T1 or T2 N0 M0), and 24% not classifiable. The median testosterone concentration at baseline was 440 ng/dL.

The major efficacy outcome measure was medical castration rate, defined as achieving and maintaining serum testosterone suppression to ≤ 50 ng/dL by Week 4 through Week 48 of treatment. Following the first injection of CAMCEVI, serum testosterone levels were suppressed to ≤ 50 ng/dL by Week 4 (+/-7 days) in 98.5% of the patients; and from Week 4 through Week 48 in 97.0% of patients (95% CI: 92.2-98.9) estimated using the Kaplan-Meier method. The time course of percent change from baseline in testosterone suppression are shown in Figure 1. The percentage of patients with testosterone suppression to ≤ 20 ng/dL was 69.3% on Day 28.

Figure 1 CAMCEVI Mean (95% CI) Percentage Change from Baseline in Serum Testosterone Concentration Over Time (N =137)

In the clinical trial, PSA levels were monitored and were lowered on average by 51% after 4 weeks after administration of CAMCEVI, 83% after 3 months and remained suppressed throughout the 48 weeks of treatment. These PSA results should be interpreted with caution because of the heterogeneity of the patient population studied. No evidence has shown that the rapidity of PSA decline correlates with clinical benefit.

16 HOW SUPPLIED/STORAGE AND HANDLING

CAMCEVI is a sterile, off-white to pale yellow, viscous and opalescent injectable emulsion supplied in a kit as a single-dose, pre-filled syringe. CAMCEVI is available as follows:

Kit Contents | NDC
Injectable emulsion in a pre-filled syringe containing 42 mg leuprolide for subcutaneous injection, a sterile 18 gauge needle, a Point-Lok®needle protection device, and Prescribing Information. | 69448-014-63

Store CAMCEVI at 2°C–8°C (36°F–46°F). Protect CAMCEVI from light by storing in the original package until time of use. Do not freeze or shake.

Excursions permitted to room temperature 25°C (77°F) for up to 6 days.

The rubber used in syringe tip cap and plunger stopper is not made of natural rubber latex.

17 PATIENT COUNSELING INFORMATION

Hypersensitivity

- Inform patients that if they have experienced hypersensitivity with other GnRH agonist drugs like CAMCEVI, CAMCEVI is contraindicated [see Contraindications (4)].

Tumor Flare

- Inform patients that CAMCEVI can cause tumor flare during the first weeks of treatment. Inform patients that the increase in testosterone can cause an increase in urinary symptoms or pain. Advise patients to contact their healthcare provider if uretral obstruction, spinal cord compression, paralysis, or new or worsened symptoms occur after beginning CAMCEVI treatment [see Warnings and Precautions (5.1)] .

Hyperglycemia and Diabetes

- Advise patients that there is an increased risk of hyperglycemia and diabetes with CAMCEVI therapy. Inform patients that periodic monitoring for hyperglycemia and diabetes is required when being treated with CAMCEVI [see Warnings and Precautions (5.2)] .

Cardiovascular Diseases

- Inform patients that there is an increased risk of myocardial infarction, sudden cardiac death, and stroke with CAMCEVI treatment. Advise patients to immediately report signs and symptoms associated with these events to their healthcare provider for evaluation [see Warnings and Precautions (5.3)].

QT/QTc Prolongation

- Inform patients that CAMCEVI can cause QT/QTc prolongation. Advise patients to immediately contact their healthcare provider in the event of syncope, presyncopal symptoms, or cardiac palpitations [see Warnings and Precautions (5.4)].

Convulsions

- Inform patients that there is an increased risk of convulsions with CAMCEVI treatment. Advise patients to immediately contact their healthcare provider if they experience convulsions [see Warnings and Precautions (5.5)].

Severe Cutaneous Adverse Reactions

- Inform patients that severe cutaneous adverse reactions (SCARs), including Stevens-Johnson syndrome (SJS), toxic epidermal necrolysis (TEN), drug reaction with eosinophilia and systemic symptoms (DRESS), and acute generalized exanthematous pustulosis (AGEP), which may be life threatening or fatal, may occur during treatment with CAMCEVI. Advise patients to contact their healthcare provider or seek medical attention right away if they experience signs or symptoms of SCARs, e.g., a prodrome of fever, flu-like symptoms, mucosal lesions, progressive skin rash, or lymphadenopathy [see Warnings and Precautions (5.6)] .

Injection Site Reactions

- Inform patients that injection site related adverse reactions may occur such as transient burning/stinging, pain, bruising, and redness. Advise patients to contact their healthcare provider if they experience rash or severe injection site reactions [see Adverse Reactions (6.1)].

Urogenital Disorders

- Advise patients that CAMCEVI may cause impotence.

Infertility

- Inform patients that CAMCEVI may cause infertility [see Use In Specific Populations (8.3)].

Manufactured for:
Accord BioPharma Inc.
8041 Arco Corporate Drive, Suite 200
Raleigh, NC 27617, USA

By:
Fareva Pau
Fareva Pau 1, Avenue du Bearn, IDRON, 64320, France